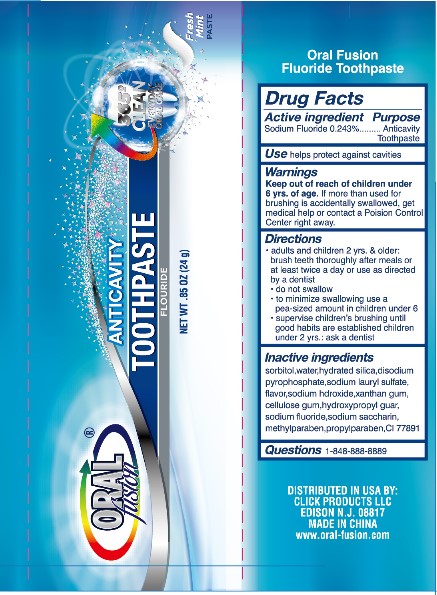 DRUG LABEL: Oral Fusion Anticavity
NDC: 70766-010 | Form: PASTE, DENTIFRICE
Manufacturer: Yangzhou SION Commodity Co.,Ltd
Category: otc | Type: HUMAN OTC DRUG LABEL
Date: 20231208

ACTIVE INGREDIENTS: SODIUM FLUORIDE 0.11 g/100 g
INACTIVE INGREDIENTS: SACCHARIN SODIUM; XANTHAN GUM; SORBITOL; METHYLPARABEN; HYDRATED SILICA; SODIUM LAURYL SULFATE; PROPYLPARABEN; WATER; SODIUM HYDROXIDE; HYDROXYPROPYL GUAR (2500-4500 MPA.S AT 1%); SODIUM PYROPHOSPHATE

70766-010

Active ingredients

Sodium Fluoride 0.243%

Purpose

anticavity

Uses

Help protect against cavities

Warnings

Keep out of the reach of children under 6 years of age. If more than used for brushing is accidently swallowed,get medical help or contact a Poison Control Center immediately.

Keep out of reach of children.

Directions

Adult and children 2 years of age and older:

- Brush teeth thoroughly after meal or at least twice a day, or use as directed by a dentist.

- Do not swallow
- To minimizing swallowing, use only a pea sized amount in children under 6
- and supervise children's brushing and rinsing to minimize swallowing.

Under 2 years:

- Ask a dentist

INACTIVE INGREDIENT

Sorbitol, Water, Hydrated Silica, Disodium pyrophosphate, Flavor, Sodium Hydroxide, Xanthan Gum, Cellulose Gum, Hydroxypropyl Guar, Methyl Paraben Sodium, Propyl Paraben Sodium, Sodium Saccharin, Water, Sodium Lauryl Sulfate, CI 778891